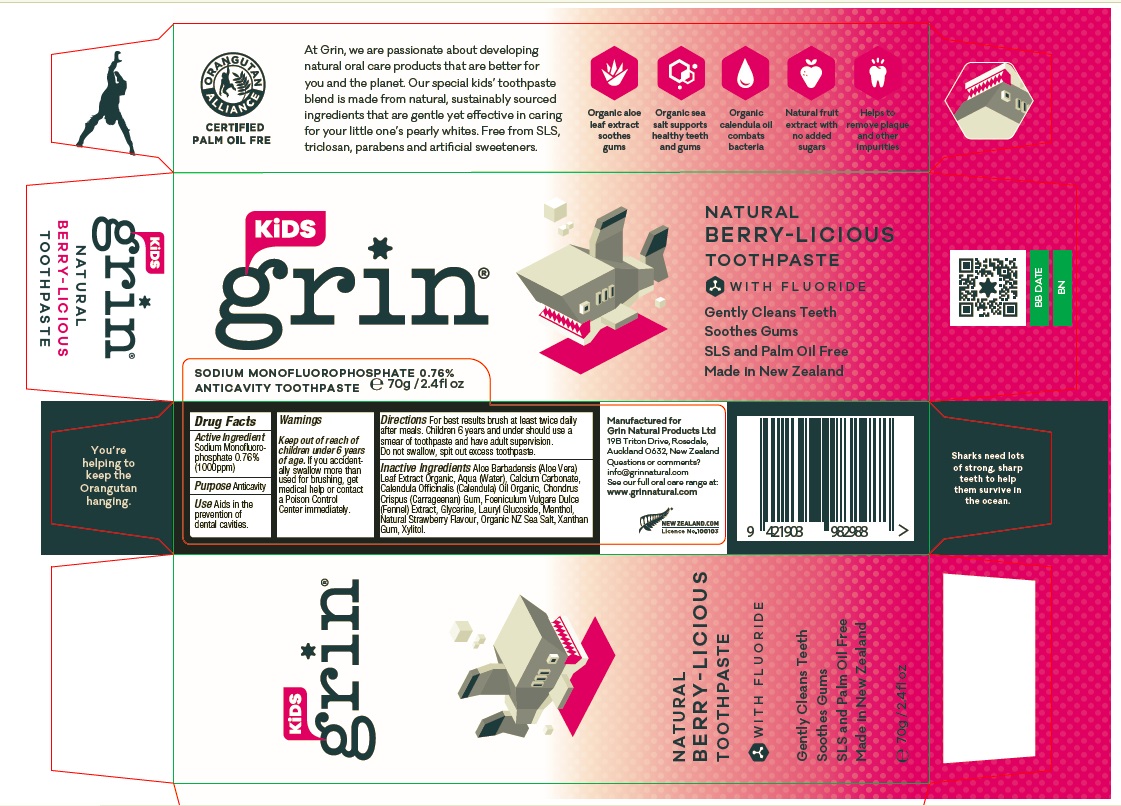 DRUG LABEL: Grin Kids
NDC: 78420-001 | Form: PASTE
Manufacturer: GRIN NATURAL PRODUCTS LIMITED
Category: otc | Type: HUMAN OTC DRUG LABEL
Date: 20200630

ACTIVE INGREDIENTS: SODIUM MONOFLUOROPHOSPHATE 0.76 g/100 g
INACTIVE INGREDIENTS: CALCIUM CARBONATE; GLYCERIN; WATER; XYLITOL; LAURYL GLUCOSIDE; ALOE VERA LEAF; CALENDULA OFFICINALIS SEED OIL; CHONDRUS CRISPUS CARRAGEENAN; FOENICULUM VULGARE FRUIT; SEA SALT; MENTHOL; XANTHAN GUM; STRAWBERRY

Active Ingredient

Sodium Monofluorophosphate 0.76% (1000ppm)

Purpose

Anticavity

Use

Aids in the prevention of dental cavities.

Keep out of reach of children under 6 years of age.

Warnings

If you accidentally swallow more than used for brushing, get medical help or contact a Poison Control Center immediately.

Directions

For best results brush at least twice daily after meals. Children 6 years and under should use a smear of toothpaste and have adult supervision.
Do not swallow, spit out excess toothpaste.

Inactive ingredients

Aloe Barbadensis (Aloe Vera) Leaf Extract Organic, Aqua (Water), Calcium Carbonate, Calendula Officinalis (Calendula) Oil Organic, Chondrus Crispus (Carrageenan) Gum, Foeniculum Vulgare Dulce (Fennel) Extract, Glycerine, Lauryl Glucoside, Menthol, Natural Strawberry Flavour, Organic NZ Sea Salt, Xanthan Gum, Xylitol.